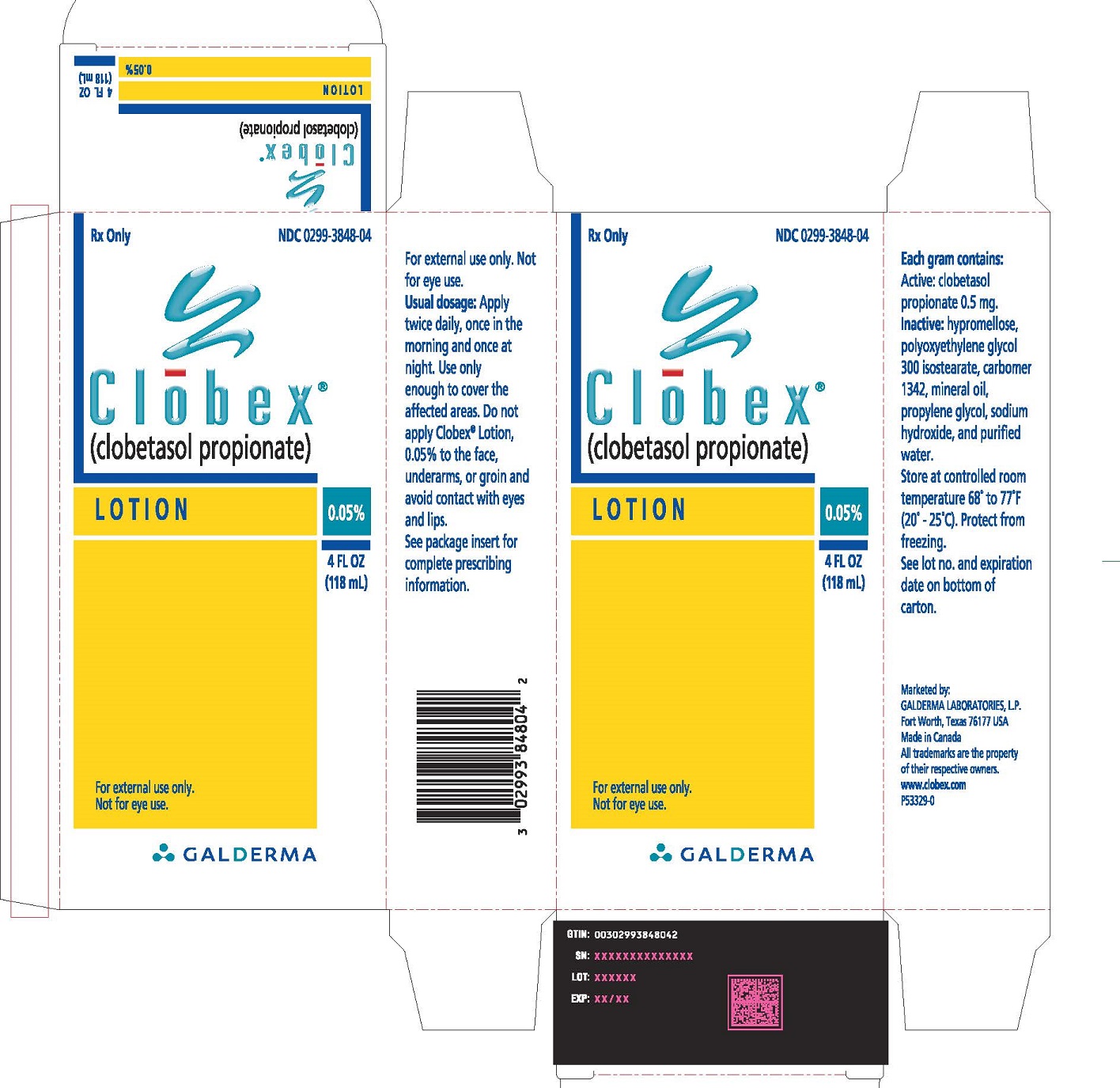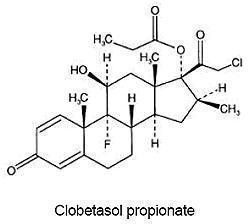 DRUG LABEL: Clobex
NDC: 0299-3848 | Form: LOTION
Manufacturer: Galderma Laboratories, L.P.
Category: prescription | Type: HUMAN PRESCRIPTION DRUG LABEL
Date: 20170315

ACTIVE INGREDIENTS: Clobetasol Propionate .05 g/100 mL
INACTIVE INGREDIENTS: HYPROMELLOSES; PEG-6 ISOSTEARATE; CARBOMER 1342; Mineral Oil; PROPYLENE GLYCOL; Sodium Hydroxide; Water

HIGHLIGHTS OF PRESCRIBING INFORMATION

These highlights do not include all the information needed to use CLOBEX® Lotion, safely and effectively. See full prescribing information for CLOBEX® Lotion.
CLOBEX® (clobetasol propionate) Lotion 0.05%, for topical use
Initial U.S. Approval: 1985

1 INDICATIONS AND USAGE

CLOBEX (clobetasol propionate) Lotion, 0.05% is a corticosteroid indicated for the relief of the inflammatory and pruritic manifestations of corticosteroid-responsive dermatoses, in patients 18 years of age or older. (1.1).
Limitations of Use:

- Do not use on the face, axillae or groin. (1.2)
- Do not use if atrophy is present at the treatment site. (1.2)
- Do not use for rosacea or perioral dermatitis. (1.2)

2 DOSAGE AND ADMINISTRATION

- Not for oral, ophthalmic, or intravaginal use. (2)
- CLOBEX Lotion, 0.05% should be applied directly onto the affected skin areas twice daily and rubbed in gently. (2)
- CLOBEX Lotion, 0.05% contains a super-high potent topical corticosteroid; therefore treatment should be limited to 2 weeks. For moderate to severe plaque psoriasis, treatment may be extended for additional 2 weeks for localized lesions (<10% body surface area) that have not sufficiently improved. (2)
- Total dosage should not exceed 50 g (50 mL or 1.75 fl. oz.) per week. (2)

3 DOSAGE FORMS AND STRENGTHS

Lotion, 0.05% (3)

4 CONTRAINDICATIONS

None. (4)

5 WARNINGS AND PRECAUTIONS

Clobetasol propionate is a highly potent topical corticosteroid that has been shown to suppress the hypothalamic-pituitary-adrenal (HPA) axis at the lowest doses tested. (5.1)
Cushing’s syndrome, hyperglycemia, and unmasking of latent diabetes mellitus can also result from systemic absorption of topical corticosteroids. (5.1)
Systemic absorption may require periodic evaluation for HPA axis suppression. Modify use if HPA axis suppression develops. (5.1)
Children may be more susceptible to systemic toxicity from use of topical corticosteroids. (5.1, 8.4)
Local adverse reactions with topical corticosteroids may occur more frequently with the use of occlusive dressings and higher potency corticosteroids, including clobetasol propionate. These reactions include: folliculitis, acneiform eruptions, hypopigmentation, perioral dermatitis, allergic contact dermatitis, secondary infection, striae and miliaria. (5.2)

6 ADVERSE REACTIONS

The most common adverse reactions (incidence > 1%) are skin atrophy, telangiectasia, discomfort skin and skin dry. (6.1)
To report SUSPECTED ADVERSE REACTIONS, contact Galderma Laboratories, L.P. at 1-866-735-4137 or FDA at 1-800-FDA-1088 or www.fda.gov/medwatch.

FULL PRESCRIBING INFORMATION

1 INDICATIONS AND USAGE

1.1 Indication

CLOBEX Lotion, 0.05% is a super-high potent topical corticosteroid formulation indicated for the relief of the inflammatory and pruritic manifestations of corticosteroid-responsive dermatoses only in patients 18 years of age or older. Treatment should be limited to 2 consecutive weeks. For moderate to severe plaque psoriasis, treatment may be extended for an additional 2 weeks for localized lesions (less than 10% body surface area) that have not sufficiently improved after the initial 2-week treatment. Any additional benefits of extending treatment should be weighed against the risk of hypothalamic-pituitary-adrenal (HPA) axis suppression before prescribing for more than 2 weeks. The total dosage should not exceed 50 g (50 mL or 1.75 fl. oz.) per week.
Patients should be instructed to use CLOBEX Lotion, 0.05% for the minimum amount of time necessary to achieve the desired results [see Dosage and Administration (2)].
Use in patients under 18 years of age is not recommended due to numerically high rates of HPA axis suppression [see Warnings and Precautions (5.1) and Use in Specific Populations (8.4)].

1.2 Limitations of Use

CLOBEX Lotion, 0.05% should not be used on the face, axillae, or groin and should not be used if there is atrophy at the treatment site. CLOBEX Lotion, 0.05% should not be used in the treatment of rosacea or perioral dermatitis.

2 DOSAGE AND ADMINISTRATION

CLOBEX Lotion, 0.05% is for topical use only, and not for ophthalmic, oral or intravaginal use.
CLOBEX Lotion, 0.05% should be applied to the affected skin areas twice daily and rubbed in gently and completely.
The total dosage should not exceed 50 g (50 mL or 1.75 fl. oz.) per week because of the potential for the drug to suppress the hypothalamic-pituitary-adrenal (HPA) axis.
CLOBEX Lotion, 0.05% contains a topical corticosteroid; therefore treatment should be limited to 2 consecutive weeks for the relief of the inflammatory and pruritic manifestations of corticosteroid-responsive dermatoses and up to 2 additional weeks in localized lesions (less than 10% body surface area) of moderate to severe plaque psoriasis that have not sufficiently improved after the initial 2 weeks of treatment with CLOBEX Lotion, 0.05%.
Unless directed by physician, CLOBEX Lotion, 0.05% should not be used with occlusive dressings.

3 DOSAGE FORMS AND STRENGTHS

Lotion, 0.05% w/w. Each gram of CLOBEX Lotion, 0.05%, contains 0.5 mg of clobestasol propionate in a white liquid.

4 CONTRAINDICATIONS

None

5 WARNINGS AND PRECAUTIONS

5.1 Effect on the Endocrine System

Clobetasol propionate is a highly potent topical corticosteroid that has been shown to suppress the HPA axis at the lowest doses tested.

Systemic absorption of topical corticosteroids has caused reversible adrenal suppression with the potential for clinical glucocorticosteroid insufficiency after withdrawal of treatment. This may occur during treatment of upon withdrawal of the topical corticosteroid.

The effect of CLOBEX Lotion, 0.05% on HPA axis function was compared to clobetasol propionate cream 0.05% (Temovate E® Emollient, 0.05%) in adults in two trials, one for psoriasis and one for atopic dermatitis. In total, 8 of 10 evaluable subjects with moderate to severe plaque psoriasis experienced adrenal suppression following 4 weeks of CLOBEX Lotion, 0.05% therapy (treatment beyond 4 consecutive weeks is not recommended in moderate to severe plaque psoriasis.) In follow-up testing, 1 of 2 subjects remained suppressed after 8 days. In this comparative trial, for clobetasol propionate cream, 0.05% there were 3 of 10 evaluable subjects with HPA axis suppression.

Furthermore, 5 of 9 evaluable subjects with moderate to severe atopic dermatitis experienced adrenal suppression following 2 weeks of CLOBEX Lotion, 0.05% therapy (treatment beyond 2 consecutive weeks is not recommended in moderate to severe atopic dermatitis). Of the 3 subjects that had follow-up testing, one subject failed to recover adrenal function 7 days post-treatment. For subjects treated with clobetasol propionate cream, 0.05%, 4 of 9 evaluable subjects experienced adrenal suppression following 2 weeks of treatment. Of the 2 subjects that had follow-up testing, both recovered adrenal function 7 days post-treatment. The proportion of subjects suppressed may be underestimated because the adrenal glands were stimulated weekly with cosyntropin in these trials.

Because of the potential for systemic absorption, use of topical corticosteroids may require that patients be periodically evaluated for HPA axis suppression. Factors that predispose a patient using a topical corticosteroid to HPA axis suppression include the use of more potent steroids, use over large surface areas, use over prolonged periods, use under occlusion, use on an altered skin barrier, and use in patients with liver failure.

An adrenocorticotropic hormone (ACTH) stimulation test may be helpful in evaluating patients for HPA axis suppression. If HPA axis suppression is documented, an attempt should be made to gradually withdraw the drug, to reduce the frequency of application, or to substitute a less potent steroid. Manifestations of adrenal insufficiency may require supplemental systemic corticosteroids. Recovery of HPA axis function is generally prompt and complete upon discontinuation of topical corticosteroids.

Cushing’s syndrome, hyperglycemia, and unmasking of latent diabetes mellitus can also result from systemic absorption of topical corticosteroids. Use of more than one corticosteroid-containing product at the same time may increase the total systemic exposure.

Pediatric patients may be more susceptible to systemic toxicity from use of topical corticosteroids. Use in patients under 18 years of age is not recommended due to numerically high rates of HPA axis suppression [see Use in Specific Populations (8.4)].

5.2 Local Adverse Reactions with Topical Corticosteroids

Local adverse reactions may occur more frequently with the use of occlusive dressings and higher potency corticosteroids, including clobetasol propionate. These reactions are listed in an approximate decreasing order of occurrence: folliculitis, acneiform eruptions, hypopigmentation, perioral dermatitis, allergic contact dermatitis, secondary infection, striae, miliaria, skin atrophy and telangiectasia. Some local adverse reactions may be irreversible. Clobetasol propionate is not recommended in patients with acne vulgaris, rosacea or perioral dermatitis.

5.3 Allergic Contact Dermatitis

Allergic contact dermatitis to any component of topical corticosteroids is usually diagnosed by a failure to heal rather than a clinical exacerbation. Clinical diagnosis of allergic contact dermatitis can be confirmed by patch testing.

5.4 Concomitant Skin Infections

In the presence of dermatologic infections, the use of an appropriate antifungal or antibacterial agent should be instituted. If a favorable response does not occur promptly, use of CLOBEX Lotion, 0.05%, should be discontinued until the infection has been adequately controlled.

6 ADVERSE REACTIONS

6.1 Clinical Trials Experience

Because clinical trials are conducted under widely varying conditions, adverse reaction rates observed in the clinical trials of a drug cannot be directly compared to rates in the clinical trials of another drug and may not reflect the rates observed in practice.
In controlled, clinical trials with CLOBEX Lotion, 0.05%, the following adverse reactions have been reported: burning/stinging, skin dryness, irritation, erythema, folliculitis, pruritus, skin atrophy, and telangiectasia. The pooled incidence of local adverse reactions in trials for psoriasis and atopic dermatitis with CLOBEX Lotion, 0.05% at 1% or greater was:

Table 1: Adverse Reactions with Incidence ≥ 1% in Clinical Trials
Adverse Reaction | Incidence
Skin Atrophy | 4.2%
Telangiectasia | 3.2%
Discomfort Skin | 1.3%
Skin Dry | 1.0%

Most local adverse events were rated as mild to moderate and they are not affected by age, race or gender.
Systemic absorption of topical corticosteroids has produced hypothalamic-pituitary-adrenal (HPA) axis suppression, manifestations of Cushing's syndrome, hyperglycemia, and glucosuria in some patients.

6.2 Postmarketing Experience

Because these reactions are reported voluntarily from a population of uncertain size, it is not always possible to reliably estimate their frequency or establish a causal relationship to drug exposure.
The following adverse reactions have been identified during post-approval use of CLOBEX Lotion, 0.05%.

- Endocrine disorders: Cushing’s syndrome, Adrenal suppression
- Skin: Rash, Pain of skin, Skin exfoliation, Skin chapped, Scaling, Induration/papulation, Lichenification.
- Other: Psoriasis (aggravation), Plaque Elevation, Excoriation.

8 USE IN SPECIFIC POPULATIONS

8.1 Pregnancy

Teratogenic Effects: Pregnancy Category C:
There are no adequate and well-controlled studies in pregnant women. Therefore, CLOBEX Lotion, 0.05% should be used during pregnancy only if the potential benefit justifies the potential risk to the fetus.
Corticosteroids have been shown to be teratogenic in laboratory animals when administered systemically at relatively low dosage levels. Some corticosteroids have been shown to be teratogenic after dermal application to laboratory animals.
Clobetasol propionate is absorbed percutaneously, and when administered subcutaneously it was a significant teratogen in both the rabbit and the mouse.
Clobetasol propionate has greater teratogenic potential than steroids that are less potent.
The effect of clobetasol propionate on pregnancy outcome and development of offspring was studied in the rat. Clobetasol propionate was administered subcutaneously to female rats twice daily (0, 12.5, 25, and 50 μg/kg/day) from day 7 of presumed gestation through day 25 of lactation or day 24 presumed gestation for those rats that did not deliver a litter. The maternal no-observed-effect level (NOEL) for clobetasol propionate was less than 12.5 μg/kg/day due to reduced body weight gain and feed consumption during the gestation period. The reproductive NOEL in the dams was 25 μg/kg/day (ratio of animal dose to proposed human dose of 0.07 on a mg/m^2/day basis) based on prolonged delivery at a higher dose level. The no-observed-adverse-effect-level (NOAEL) for viability and growth in the offspring was 12.5 μg/kg/day (ratio of animal dose to proposed human dose of 0.03 on a mg/m^2/day basis) based on incidence of stillbirths, reductions in pup body weights on days 1 and 7 of lactation, increased pup mortality, increases in the incidence of umbilical hernia, and increases in the incidence of pups with cysts on the kidney at higher dose levels during the preweaning period. The weights of the epididymides and testes were significantly reduced at higher dosages. Despite these changes, there were no effects on the mating and fertility of the offspring.

8.3 Nursing Mothers

Systemically administered corticosteroids appear in human milk and could suppress growth, interfere with endogenous corticosteroid production, or cause other untoward effects. It is not known whether topical administration of corticosteroids could result in sufficient systemic absorption to produce detectable quantities in breast milk. Because many drugs are excreted in human milk, caution should be exercised when CLOBEX Lotion, 0.05% is administered to a nursing woman.

8.4 Pediatric Use

Use of CLOBEX Lotion, 0.05% in pediatric patients is not recommended due to the potential for HPA axis suppression [see Warnings and Precautions (5.1)].
The HPA axis suppression potential of CLOBEX Lotion, 0.05% has been studied in adolescents (12 to 17 years of age) with moderate to severe atopic dermatitis covering a minimum of 20% of the total body surface area. In total 14 subjects were evaluated for HPA axis function. Subjects were treated twice daily for 2 weeks with CLOBEX Lotion, 0.05%. After 2 weeks of treatment, 9 out of 14 of the subjects experienced adrenal suppression. One out of 4 subjects treated with CLOBEX Lotion, 0.05% who were retested remained suppressed two weeks post-treatment. In comparison, 2 of 10 subjects treated with clobetasol propionate cream, 0.05% demonstrated HPA axis suppression. One subject who was retested recovered.
None of the subjects who developed HPA axis suppression had concomitant clinical signs of adrenal suppression and none of them was discontinued from the study for reasons related to the safety or tolerability of CLOBEX Lotion, 0.05%. However patients with acute illness or injury may have increased morbidity and mortality with intermittent HPA axis suppression.
Because of higher ratio of skin surface area to body mass, pediatric patients are at a greater risk than adults of HPA axis suppression and Cushing’s syndrome when they are treated with topical corticosteroids. They are therefore also at greater risk of glucocorticosteroid insufficiency during and/or after withdrawal of treatment. Adverse effects including striae have been reported with inappropriate use of topical corticosteroids in infants and children.
HPA axis suppression, Cushing’s syndrome, linear growth retardation, delayed weight gain, and intracranial hypertension have been reported in children receiving topical corticosteroids. Manifestations of adrenal suppression in children include low plasma cortisol levels and absence of response to ACTH stimulation. Manifestations of intracranial hypertension include bulging fontanelles, headaches, and bilateral papilledema.

8.5 Geriatric Use

Clinical studies of CLOBEX Lotion, 0.05% did not include sufficient numbers of subjects aged 65 and over to adequately determine whether they respond differently than younger subjects. In general, dose selection for an elderly patient should be made with caution, usually starting at the low end of the dosing range, reflecting the greater frequency of decreased hepatic, renal or cardiac function, and of concomitant disease or other drug therapy.

10 OVERDOSAGE

Topically applied CLOBEX Lotion, 0.05% can be absorbed in sufficient amount to produce systemic effects [see Warnings and Precautions (5.1)].

11 DESCRIPTION

CLOBEX (clobetasol propionate) Lotion, 0.05% contains clobetasol propionate, a synthetic fluorinated corticosteroid, for topical use. The corticosteroids constitute a class of primarily synthetic steroids used topically as anti-inflammatory and antipruritic agents. Clobetasol propionate is 21-chloro-9-fluoro-11β, 17-dihydroxy-16β -methylpregna-1,4-diene-3,20-dione 17-propionate, with the empirical formula C25H32CIFO5, and a molecular weight of 466.98 (CAS Registry Number 25122-46-7).
The following is the chemical structure:

Clobetasol propionate is a white to almost white crystalline powder that is practically insoluble in water. Each gram of CLOBEX Lotion, 0.05% contains 0.5 mg of clobetasol propionate, in a white liquid composed of hypromellose, propylene glycol, mineral oil, polyoxyethylene glycol 300 isostearate, carbomer 1342, sodium hydroxide and purified water.

12 CLINICAL PHARMACOLOGY

12.1 Mechanism of Action

Like other topical corticosteroids CLOBEX Lotion, 0.05% has anti-inflammatory, antipruritic, and vasoconstrictive properties. The mechanism of the anti-inflammatory activity of the topical steroids in general is unclear. However, corticosteroids are thought to act by induction of phospholipase A2 inhibitory proteins, collectively called lipocortins. It is postulated that these proteins control the biosynthesis of potent mediators of inflammation such as prostaglandins and leukotrienes by inhibiting the release of their common precursor, arachidonic acid. Arachidonic acid is released from membrane phospholipids by phospholipase A2.

12.2 Pharmacodynamics

Vasoconstrictor Assay
CLOBEX Lotion, 0.05% is in the super-high range of potency as demonstrated in vasoconstrictor studies in healthy subjects when compared with other topical corticosteroids. However, similar blanching scores do not necessarily imply therapeutic equivalence.
Hypothalamic-Pituitary-Adrenal (HPA) Axis Suppression
In studies evaluating the potential for hypothalamic-pituitary-adrenal (HPA) axis suppression, CLOBEX Lotion, 0.05% demonstrated rates of suppression that were numerically higher than those of a clobetasol propionate 0.05% cream (Temovate E® Emollient, 0.05%), [see Warnings and Precautions (5.1) and Use in Specific Population (8.4)].

12.3 Pharmacokinetics

The extent of percutaneous absorption of topical corticosteroids is determined by many factors, including the vehicle, the integrity of the epidermal barrier and occlusion.
Topical corticosteroids can be absorbed from normal intact skin. Inflammation and other disease processes in the skin may increase percutaneous absorption.
There are no human data regarding the distribution of corticosteroids to body organs following topical application. Nevertheless, once absorbed through the skin, topical corticosteroids are handled through metabolic pathways similar to systemically administered corticosteroids. They are metabolized, primarily in the liver, and are then excreted by the kidneys. In addition, some corticosteroids and their metabolites are also excreted in the bile.

13 NONCLINICAL TOXICOLOGY

13.1 Carcinogenesis, Mutagenesis, Impairment of Fertility

Clobetasol propionate was not carcinogenic to rats when topically applied for 2 years at concentrations up to 0.005% which corresponded to doses up to 11 µg/kg/day (ratio of animal dose to proposed human dose of 0.03 on a mg/m^2/day basis).
Clobetasol propionate at concentrations up to 0.001% did not increase the rate of formation of ultra violet light-induced skin tumors when topically applied to hairless mice 5 days per week for a period of 40 weeks.
Clobetasol propionate was negative in the in vitro mammalian chromosomal aberration test and in the in vivo mammalian erythrocyte micronucleus test.
The effect of subcutaneously administered clobetasol propionate on fertility and general reproductive toxicity was studied in rats at doses of 0, 12.5, 25, and 50 µg/kg/day. Males were treated beginning 70 days before mating and females beginning 15 days before mating through day 7 of gestation. A dosage level of less than 12.5 µg/kg/day clobetasol propionate was considered to be the no-observed-effect-level (NOEL) for paternal and maternal general toxicity based on decreased weight gain and for male reproductive toxicity based on increased weights of the seminal vesicles. The female reproductive NOEL was 12.5 µg/kg/day (ratio of animal dose to proposed human dose of 0.03 on a mg/m^2/day basis) based on reduction in the numbers of estrous cycles during the pre-cohabitation period and an increase in the number of nonviable embryos at higher doses.

14 CLINICAL STUDIES

The efficacy of CLOBEX Lotion, 0.05% in psoriasis and atopic dermatitis has been demonstrated in two adequate and well-controlled clinical trials. The first trial was conducted in subjects with moderate to severe plaque psoriasis. Subjects were treated twice daily for 4 weeks with either CLOBEX Lotion, 0.05% or vehicle lotion. Trial results demonstrated that the efficacy of CLOBEX Lotion, 0.05% in treating moderate to severe plaque psoriasis was superior to that of vehicle.
At the end of treatment (4 weeks), 30 of 82 subjects (36.6%) treated with CLOBEX Lotion, 0.05% compared with 0 of 29 (0%) treated with vehicle achieved success. Success was defined as a score of none or very mild (no or very slight clinical signs or symptoms of erythema, plaque elevation, or scaling) on the Global Severity scale of psoriasis.
The second trial was conducted in subjects with moderate to severe atopic dermatitis. Subjects were treated twice daily for 2 weeks with either CLOBEX Lotion, 0.05% or vehicle lotion. Trial results demonstrated that the efficacy of CLOBEX Lotion, 0.05% in treating moderate to severe atopic dermatitis was superior to that of vehicle.
At the end of treatment (2 weeks), 41 of 96 subjects (42.7%) treated with CLOBEX Lotion, 0.05% compared with 4 of 33 (12.1%) treated with vehicle achieved success. Success was defined as a score of none or very mild (no or very slight clinical signs or symptoms of erythema, induration/papulation, oozing/crusting, or pruritus) on the Global Severity scale of atopic dermatitis.

16 HOW SUPPLIED/STORAGE AND HANDLING

CLOBEX Lotion, 0.05% is a white liquid, supplied in the following sizes:

2 fl oz/59 mL NDC 0299-3848-02 high density polyethylene bottles

4 fl oz/118 mL NDC 0299-3848-04 high density polyethylene bottles

Store at USP controlled room temperature 68° to 77°F (20°-25°C), with excursions permitted between 59° and 86°F (15° - 30°C). Protect from freezing.

17 PATIENT COUNSELING INFORMATION

See FDA-approved patient labeling (Patient Information)

Information for Patients

Inform the patient using toical corticosteroids to adhere to the following instructions:

- This medication is to be used as directed by the physician and should not be used longer than the prescribed time period.
- This medication should not be used for any disorder other than that for which it was prescribed.
- Do not use other corticosteroid-containing products while using CLOBEX (clobetasol propionate) Lotion, 0.05%.
- The treated skin area should not be bandaged, otherwise covered, or wrapped so as to be occlusive unless directed by the physician.
- Patients should wash their hands after applying the medication.
- Patients should report any signs of local or systemic adverse reactions to the physician.
- Patients should inform their physicians that they are using CLOBEX (clobetasol propionate) Lotion, 0.05% if surgery is contemplated.
- This medication is for external use only. It should not be used on the face, underarms, or groin area, and avoid contact with the eyes and lips.
- As with other corticosteroids, therapy should be discontinued when control is achieved. If no improvement is seen within 2 weeks, contact the physician.
- Patients should be informed to not use more than 50 g (50 mL or 1.75 fl. oz.) per week of CLOBEX Lotion, 0.05%.

Patient Information
CLOBEX® (KLO-bex)
(clobetasol propionate)
Lotion

Important: For use on skin only. Do not get CLOBEX Lotion near or in your eyes, mouth or vagina.
Read the Patient Information that comes with CLOBEX Lotion before you start using it and each time you get a refill. There may be new information. This information does not take the place of talking with your doctor about your medical condition or your treatment.
What is CLOBEX Lotion?
CLOBEX Lotion is a prescription corticosteroid medicine used to reduce the swelling (inflammation) and itching caused by certain skin conditions called corticosteroid-responsive dermatoses, including atopic dermatitis and psoriasis, in people 18 years of age and older. CLOBEX Lotion is for use on the skin only (topical).

- CLOBEX Lotion should only be used for the shortest amount of time needed to treat your skin condition.
- CLOBEX Lotion should not be used for more than 2 weeks in a row unless your doctor tells you to use it for a longer time.
- You should not apply more than 50 mL (1.75 fluid ounces) of CLOBEX Lotion to your skin in 1 week.

You should not use CLOBEX Lotion:

- on your face, underarms (armpits), or groin areas
- if you have thinning of the skin (atrophy) at the treatment site
- to treat rosacea or a rash around your mouth (perioral dermatitis)

CLOBEX Lotion should not be used in children under 18 years of age.
What should I tell my doctor before using CLOBEX Lotion?
Before you use CLOBEX Lotion, tell your doctor if you:

- have a skin infection. You may need medicine to treat the skin infection before you use CLOBEX Lotion.
- have any open sores or cuts on your skin
- plan to have surgery
- have any other medical conditions
- are pregnant or plan to become pregnant. It is not known if CLOBEX Lotion can harm your unborn baby.
- are breast-feeding or plan to breast-feed. It is not known if CLOBEX Lotion passes into your breast milk. Talk to your doctor about the best way to feed your baby if you use CLOBEX Lotion.

Tell your doctor about all the medicines you take, including prescription and non-prescription medicines, vitamins, and herbal supplements. Especially tell your doctor if you take other corticosteroid medicines by mouth or use other products on your skin that contain corticosteroids. You should not use other products that contain corticosteroids while you are using CLOBEX Lotion. Ask your doctor or pharmacist if you are not sure.
Know the medicines you take. Keep a list of them to show your doctor and pharmacist when you get a new medicine.
How should I use CLOBEX Lotion?

- Use CLOBEX Lotion exactly as your doctor tells you to use it.
- Your doctor should tell you how much CLOBEX Lotion to use and where to apply it.
- CLOBEX Lotion is for skin use only (topical).
- You should not use CLOBEX Lotion on your face, underarms or groin. Avoid getting CLOBEX Lotion in your eyes or on your lips.
- Apply CLOBEX Lotion 2 times each day.
- Apply only enough CLOBEX Lotion to cover your affected skin areas.

To apply CLOBEX Lotion:

- Turn the bottle of CLOBEX Lotion upside down.
- Apply CLOBEX Lotion onto your fingertips or directly on your affected skin area.
- Rub CLOBEX Lotion into your affected skin area gently and completely.
- Repeat these steps to apply CLOBEX Lotion to all affected skin areas as your doctor tells you.
- Wash your hands after applying CLOBEX Lotion.
- Do not bandage, cover or wrap your treated areas unless your doctor tells you to.
- Tell your doctor if your skin condition is not getting better after using CLOBEX Lotion for 2 weeks in a row. Do not use CLOBEX Lotion for more than 2 weeks unless your doctor tells you to.

What are the possible side effects of CLOBEX Lotion?
CLOBEX Lotion can pass through your skin. Too much CLOBEX Lotion passing through your skin can cause your adrenal glands to stop working. Your doctor may do blood tests to check how well your adrenal glands are working.
The most common side effects of CLOBEX Lotion include:

- burning, stinging, itching, redness, irritation and dry skin
- thinning of the skin
- widening of small blood vessels in the skin
- skin discomfort at the site of application

If you go to another doctor for illness, injury or surgery tell your doctor that you are using CLOBEX Lotion.
Tell your doctor if you have any side effect that bothers you or that does not go away.
These are not all the possible side effects of CLOBEX Lotion. For more information, ask your doctor or pharmacist.
Call your doctor for medical advice about side effects. You may report side effects to FDA at 1-800-FDA-1088.
You may also report side effects to Galderma Laboratories, L.P. at 1-866-735-4137.
How should I store CLOBEX Lotion?

- Store CLOBEX Lotion at room temperature between 68°F to 77°F (20°C to 25°C).
- Do not freeze CLOBEX Lotion.

Keep CLOBEX Lotion and all medicines out of reach of children.
General information about CLOBEX Lotion.
Medicines are sometimes prescribed for purposes other than those listed in a Patient Information leaflet. Do not use CLOBEX Lotion for a condition for which it was not prescribed. Do not give CLOBEX Lotion to other people, even if they have the same symptoms that you have. It may harm them.
This Patient Information leaflet summarizes the most important information about CLOBEX Lotion. If you would like more information, talk with your doctor. You can ask your pharmacist or doctor for information about CLOBEX Lotion that is written for health professionals.
What are the ingredients in CLOBEX Lotion?
Active ingredient: clobetasol propionate
Inactive ingredients: hypromellose, propylene glycol, mineral oil, polyoxyethylene glycol 300 isostearate, carbomer 1342, sodium hydroxide and purified water.
This Patient Information has been approved by the U.S. Food and Drug Administration.
Marketed by:
GALDERMA LABORATORIES, L.P.
Fort Worth, Texas 76177 USA
Made in Canada
P53324-0
Revised 03/2017

PACKAGE LABEL.PRINCIPAL DISPLAY PANEL

Rx Only
NDC 0299-3848-04
CLOBEX® (clobetasol propionate) LOTION 0.05%
4 FL OZ (118 mL)
For external use only.
Not for eye use.
Galderma